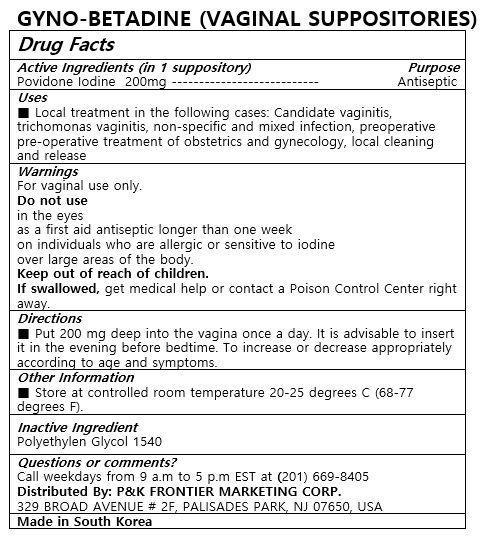 DRUG LABEL: GYNO-BETADINE
NDC: 72689-0042 | Form: SUPPOSITORY
Manufacturer: OASIS TRADING
Category: otc | Type: HUMAN OTC DRUG LABEL
Date: 20190321

ACTIVE INGREDIENTS: POVIDONE-IODINE 200 mg/1 1
INACTIVE INGREDIENTS: POLYETHYLENE GLYCOL 1500

ACTIVE INGREDIENT

POVIDONE-IODINE

PURPOSE

Local treatment in the following cases: Candidate vaginitis, trichomonas vaginitis, non-specific and mixed infection, preoperative pre-operative treatment of obstetrics and gynecology, local cleaning and release

Keep out of reach of children

INDICATIONS AND USAGE

Put 200 mg deep into the vagina once a day. It is advisable to insert it in the evening before bedtime. To increase or decrease appropriately according to age and symptoms.

Do not use
in the eyes
as a first aid antiseptic longer than one week
on individuals who are allergic or sensitive to iodine
over large areas of the body
Keep out of reach of children.
If swallowed, get medical help or contact a Poison Control Center right away.

INACTIVE INGREDIENT

POLYETHYLENE GLYCOL 1540

DOSAGE AND ADMINISTRATION

For vaginal use only